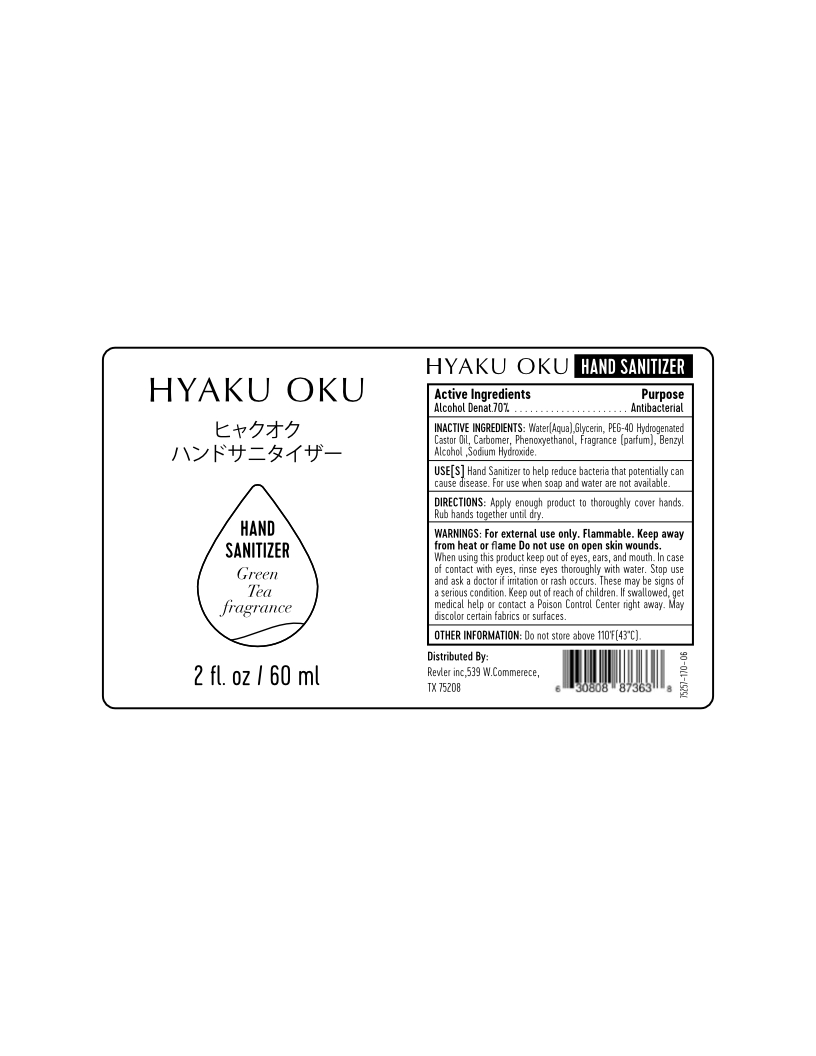 DRUG LABEL: Hand Sanitizer
NDC: 75257-170 | Form: GEL
Manufacturer: Revler, Inc
Category: otc | Type: HUMAN OTC DRUG LABEL
Date: 20200429

ACTIVE INGREDIENTS: ALCOHOL 80 mL/100 mL
INACTIVE INGREDIENTS: HYDROGENATED CASTOR OIL; CARBOMER 1342; PHENOXYETHANOL; SODIUM HYDROXIDE; GLYCERIN 1.45 mL/100 mL; WATER; BENZYL ALCOHOL

This is a hand sanitizer manufactured according to the Temporary Policy for Preparation of Certain Alcohol-Based Hand Sanitizer Products During the Public Health Emergency (CoViD-19); Guidance for Industry.

The hand sanitizer is manufactured using only the following United States Pharmacopoeia (USP) grade ingredients in the preparation of the product (percentage in final product formulation)

1. Alcohol (ethanol) (USP or Food Chemical Codex (FCC) grade) (70%, volume/volume (v/v)) in an aqueous solution denatured according to Alcohol and Tobacco Tax and Trade Bureau regulations in 27 CFR part 20.
2. Glycerol
3. Hydrogenated Castor Oil
4. Sterile distilled water or boiled cold water.
5. Carbomer
6. Phenoxyethanol
7. Benzyl Alcohol
8. Sodium Hydroxide
9. Fragrance (parfum)

The firm does not add other active or inactive ingredients. Different or additional ingredients may impact the quality and potency of the product.

Active Ingredient(s)

Alcohol 70% v/v. Purpose: Antiseptic

Purpose

Antiseptic, Hand Sanitizer

Use

Hand Sanitizer to help reduce bacteria that potentially can cause disease. For use when soap and water are not available.

Warnings

For external use only. Flammable. Keep away from heat or flame

- Do not use in on open skin wounds.

When using this product keep out of eyes, ears, and mouth. In case of contact with eyes, rinse eyes thoroughly with water.
Stop use and ask a doctor if irritation or rash occurs. These may be signs of a serious condition.
Keep out of reach of children. If swallowed, get medical help or contact a Poison Control Center right away.

Stop use and ask a doctor if irritation or rash occurs. These may be signs of a serious condition.

Keep out of reach of children. If swallowed, get medical help or contact a Poison Control Center right away.

Directions

- • Apply enough product to thoroughly cover hands. Rub hands together until dry.

RECENT MAJOR CHANGES

• Apply enough product to thoroughly cover hands. Rub hands together until dry.

Other information

- Do not store above 110'F(43"C).

Inactive ingredients

Water(Aqua),Glycerin,PEG-40 Hydrogenated Castor Oil, Carbomer, Phenoxyethanol, Fragrance (parfum), Benzyl Alcohol ,Sodium Hydroxide

Package Label - Principal Display Panel

60 mL NDC: 75257-170-06